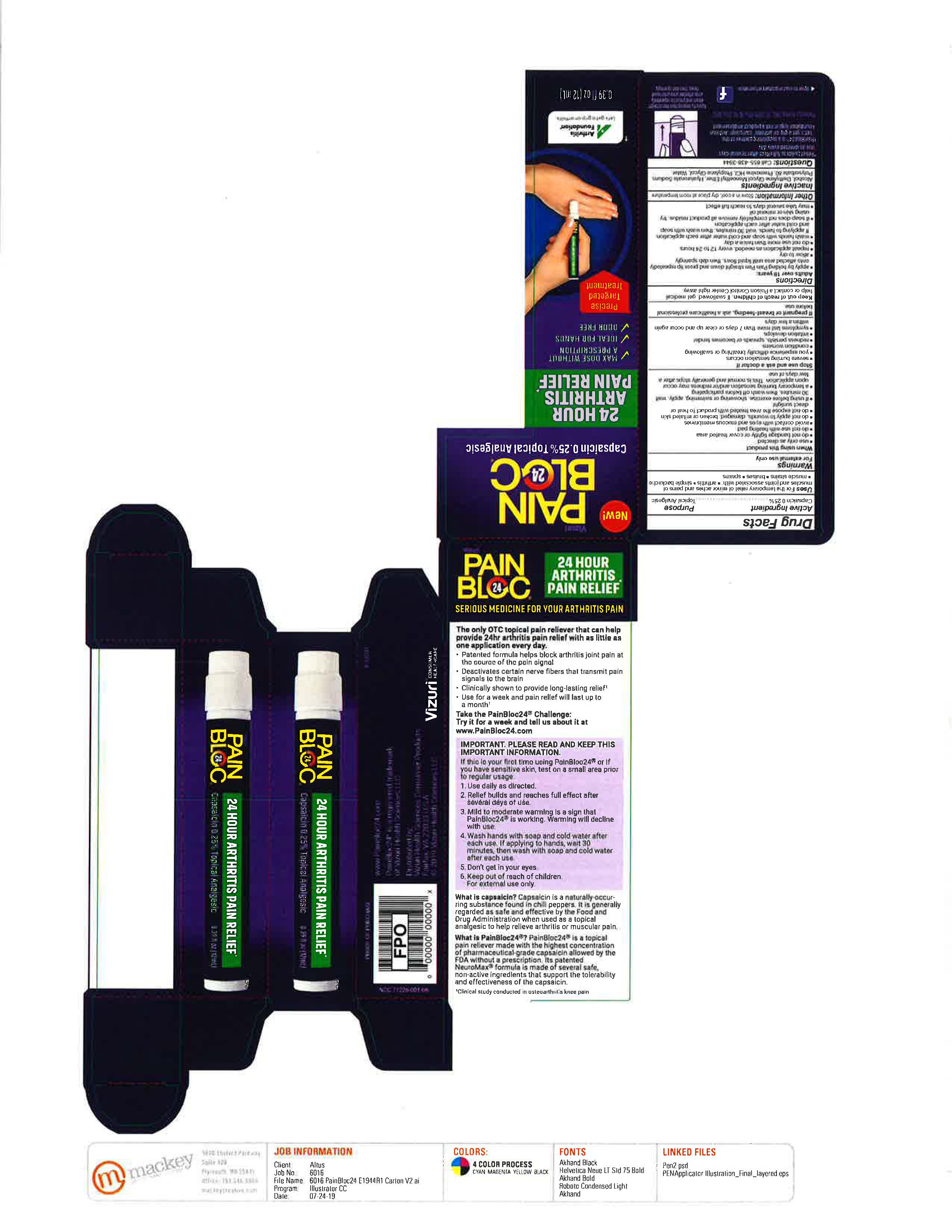 DRUG LABEL: PainBloc24
NDC: 71226-001 | Form: SOLUTION
Manufacturer: Vizuri Health Sciences LLC
Category: otc | Type: HUMAN OTC DRUG LABEL
Date: 20220104

ACTIVE INGREDIENTS: CAPSAICIN 2.5 mg/1 mL
INACTIVE INGREDIENTS: ALCOHOL; DIETHYLENE GLYCOL MONOETHYL ETHER; HYALURONATE SODIUM; POLYSORBATE 80; PROPYLENE GLYCOL; WATER; PRAMOXINE HYDROCHLORIDE

PainBloc24

Active Ingredient

Capsaicin 0.25%

Purpose

Topical Analgesic

Uses

For the temporary relief of minor aches and pains of muscles and joints associated with:

- Arthritis
- Simple backache
- Muscle strains
- Bruises
- Sprains

Warnings

For external use only

When using this product

- Use only as directed
- Do not bandage tightly or cover treated area
- Do not use with heating pad
- Avoid contact with eyes and mucous membranes
- Do not apply to wounds, damaged, broken or irritated skin
- Do not expose the area treated with product to heat or direct sunlight
- If using before exercise, showering or swimming, apply, wait 30 minutes, then wash off before participating
- A temporary burning sensation and/or redness may occur upon application. This is normal and generally stops after a few days of use

Stop use and ask a doctor if

- Severe burning sensation occurs
- You experience difficulty breathing or swallowing
- Condition worsens
- Redness persists, spreads or becomes tender
- Irritation develops
- Symptoms last more than 7 days or clear up and occur again within a few days

PREGNANCY OR BREAST FEEDING

If pregnant or breast-feeding, ask a healthcare professional before use.

Keep out of reach of children. If swallowed, get medical help or contact a Poison Control Center right away.

Directions

Adults over 18 years:

- Apply by holding Pain Pen straight down and press tip repeatedly on to affected area until liquid flows. Then dab sparingly.
- Allow to dry
- Repeat application, as needed, every 12 to 24 hours
- Do not use more than twice a day
- Wash hands with soap and water after each application. If applying to hand, wait 30minutes, then wash with soap and cold water after each application.
- If soap does not completely remove all product residues, try using skin or mineral oil.
- May take several days to reach full effect

Inactive Ingredients

Alcohol, Diethylene Glycol Monoethyl Ether, Hyaluronate Sodium, Polysorbate 80, Pramoxine HCl, Propylene Glycol, Water

Questions

Call 855-438-3944

Distributed by Vizuri Consumer Healthcare
Fairfax, VA 22033 U.S.A.